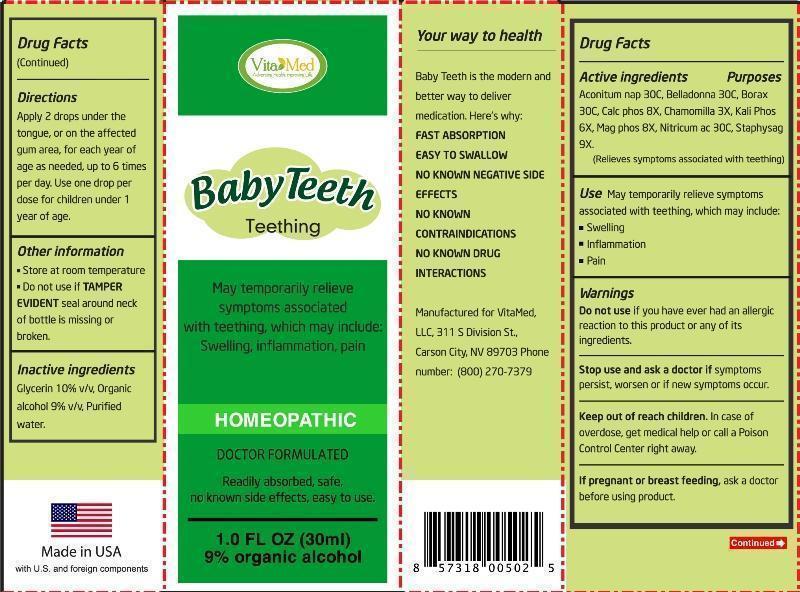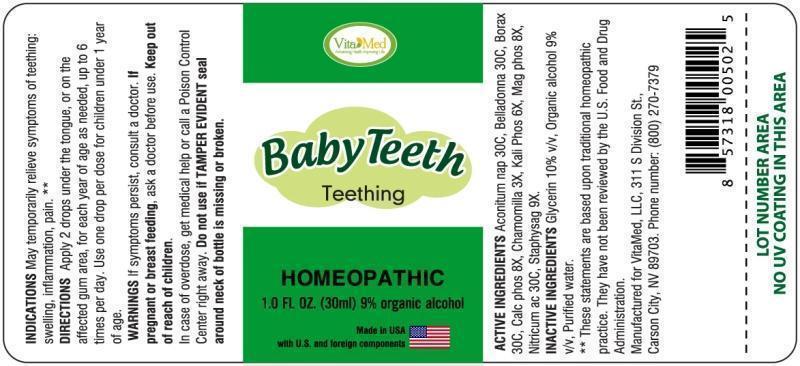 DRUG LABEL: Babyteeth
NDC: 64249-0001 | Form: LIQUID
Manufacturer: VitaMed, LLC
Category: homeopathic | Type: HUMAN OTC DRUG LABEL
Date: 20150106

ACTIVE INGREDIENTS: ACONITUM NAPELLUS 30 [hp_C]/1 mL; ATROPA BELLADONNA 30 [hp_C]/1 mL; SODIUM BORATE 30 [hp_C]/1 mL; TRIBASIC CALCIUM PHOSPHATE 8 [hp_X]/1 mL; MATRICARIA RECUTITA 3 [hp_X]/1 mL; POTASSIUM PHOSPHATE, DIBASIC 6 [hp_X]/1 mL; MAGNESIUM PHOSPHATE, DIBASIC TRIHYDRATE 8 [hp_X]/1 mL; NITRIC ACID 30 [hp_C]/1 mL; DELPHINIUM STAPHISAGRIA SEED 9 [hp_X]/1 mL
INACTIVE INGREDIENTS: WATER; ALCOHOL; GLYCERIN

DRUG FACTS:

ACTIVE INGREDIENTS:

Aconitum Napellus 30C, Belladonna 30C, Borax 30C, Calcarea Phosphorica 8X, Chamomilla 3X, Kali Phosphoricum 6X, Magnesia Phosphorica 8X, Nitricum Acidum 30C, Staphysagria 9X

INDICATIONS:

May temporarily relieve symptoms of teething: swelling, inflammation, pain.**

**These statements are based upon traditional homeopathic practice. They have not been reviewed by the U.S. Food and Drug Administration.

WARNINGS:

If symptoms persist, consult a doctor.

If pregnant or breast-feeding, ask a doctor before use.

Keep out of reach of children. In case of overdose, get medical help or call a Poison Control Center right away.

Do not use if TAMPER EVIDENT seal around neck of bottle is missing or broken.

Keep out of reach of children. In case of overdose, get medical help or call a Poison Control Center right away.

DIRECTIONS:

Apply 2 drops under the tongue, or on the affected gum area, for each year of age as needed, up to 6 times per day. Use one drop per dose for children under 1 year of age.

INDICATIONS:

May temporarily relieve symptoms of teething: swelling, inflammation, pain.**

**These statements are based upon traditional homeopathic practice. They have not been reviewed by the U.S. Food and Drug Administration.

INACTIVE INGREDIENTS:

Glycerin 10% v/v, Organic alcohol 9% v/v, Purified water.

QUESTIONS:

Manufactured for VitaMed, LLC, 311 S Division St.,

Carson City, NV 89703. Phone number: (800) 270-7379

PACKAGE LABEL DISPLAY

Vita Med

BabyTeeth

Teething

HOMEOPATHIC

1.0 FL OZ. (30 ml)

Made in USA

with U.S. and foreign components